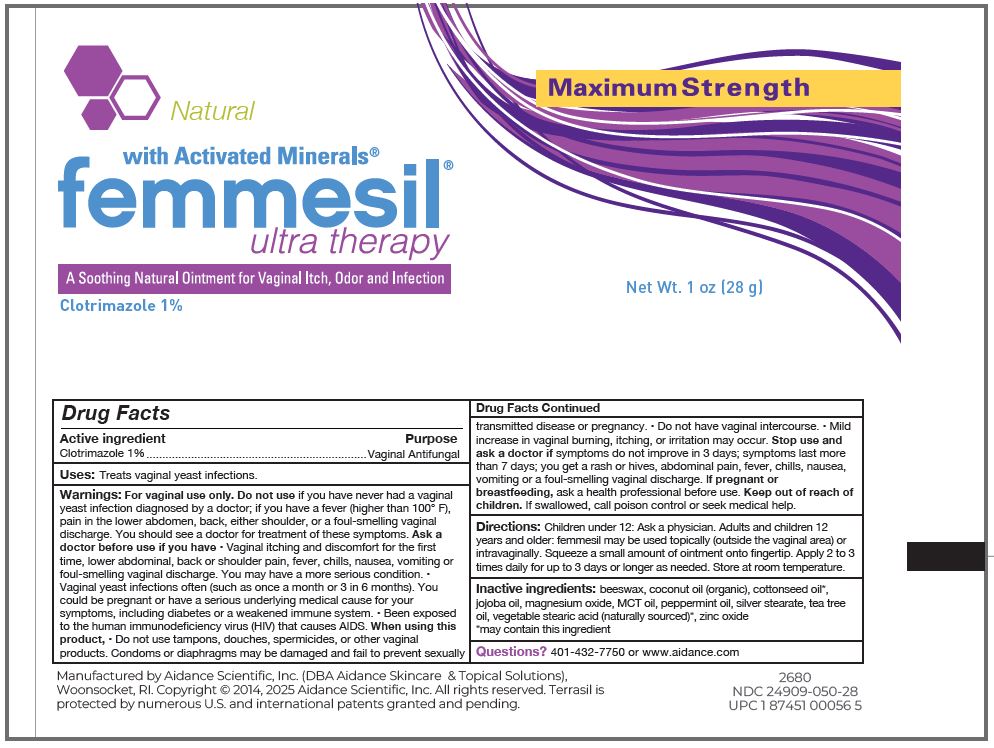 DRUG LABEL: femmesil Ultra Therapy
NDC: 24909-050 | Form: OINTMENT
Manufacturer: Aidance Scientific, Inc.
Category: otc | Type: HUMAN OTC DRUG LABEL
Date: 20250825

ACTIVE INGREDIENTS: CLOTRIMAZOLE 1 g/100 g
INACTIVE INGREDIENTS: MAGNESIUM OXIDE; JOJOBA OIL; COTTONSEED OIL; PEPPERMINT OIL; COCONUT OIL; BEESWAX; PALM OIL; ZINC OXIDE; SILVER STEARATE; TEA TREE OIL; STEARIC ACID

24909-050 femmesil Ultra Therapy Max

Active Ingredient

Clotrimazole

Purpose

Vaginal Antifungal

Uses

Treats vaginal yeast infections.

Warnings

For vaginal use only.

Do not use if you have never had a vaginal yeast infection diagnosed by a doctor; if you have a fever (higher than 100° F), pain in the lower abdomen, back, either shoulder, or a foul-smelling vaginal discharge.You should see a doctor for treatment of these symptoms.

Ask a doctor before use if you have

• Vaginal itching and discomfort for the first time, lower abdominal, back or shoulder pain, fever, chills, nausea, vomiting or foul-smelling vaginal discharge. You may have a more serious condition.

• Vaginal yeast infections often (such as once a month or 3 in 6 months). You could be pregnant or have a serious underlying medical cause for your symptoms, including diabetes or a weakened immune system.

• Been exposed to the human immunodeficiency virus (HIV) that causes AIDS.

When using this product

• Do not use tampons, douches, spermicides, or other vaginal products. Condoms or diaphragms may be damaged and fail to prevent sexually transmitted disease or pregnancy.

• Do not have vaginal intercourse.

• Mild increase in vaginal burning, itching, or irritation may occur.

Stop use and ask a doctor if symptoms do not improve in 3 days; symptoms last more than 7 days; you get a rash or hives, abdominal pain, fever, chills, nausea, vomiting or a foul-smelling vaginal discharge.

PREGNANCY OR BREAST FEEDING

If pregnant or breastfeeding, ask a health professional before use.

Keep out of reach of children.

OTHER SAFETY INFORMATION

If swallowed, call poison control or seek medical help.

Directions

Children under 12: Ask a physician. Adults and children 12 years and older: femmesil may be used topically (outside the vaginal area) or intravaginally. Squeeze a small amount of ointment onto fingertip. Apply 2 to 3 times daily for up to 3 days or longer as needed. Store at room temperature.

Inactive Ingredients

beeswax, coconut oil (organic), cottonseed oil*, jojoba oil, magnesium oxide, MCT oil, peppermint oil, silver stearate, tea tree oil, vegetable stearic acid (naturally sourced)*, zinc oxide

*may contain this ingredient

Questions?

401-432-7750 or www.aidance.com